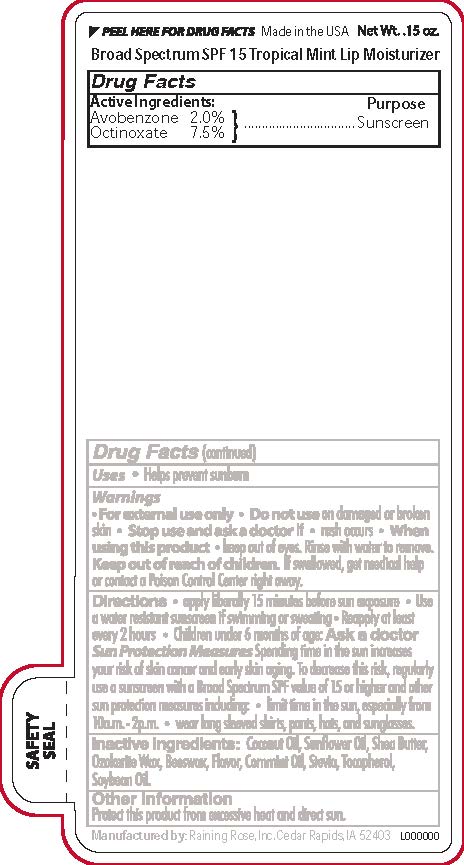 DRUG LABEL: Tropical Mint Broad Spectrum SPF 15  Lip Moisturizer
NDC: 65692-0552 | Form: STICK
Manufacturer: Raining Rose, Inc
Category: otc | Type: HUMAN OTC DRUG LABEL
Date: 20231018

ACTIVE INGREDIENTS: AVOBENZONE 0.09 g/4.25 g; OCTINOXATE 0.32 g/4.25 g
INACTIVE INGREDIENTS: MENTHA ARVENSIS LEAF OIL; SOYBEAN OIL; TOCOPHEROL; COCONUT OIL; SUNFLOWER OIL; WHITE WAX; STEVIA REBAUDIUNA LEAF; SHEA BUTTER; CERESIN

Tropical Mint SPF 15 Lip balm

Active Ingredients

Avobenzone 2.0%

Octinoxate 7.5%

Purpose

Sunscreen

Warnings

For external use only

Do not use

on damaged or broken skin.

Stop Use and ask a doctor if

Rash Occurs

When Using this Product

Keep out of eyes. Rinse well with water to remove.

Keep out of reach of children

If swallowed, get medical help or contact a Poison Control Center right away.

Directions

Apply liberally 15 minutes before sun exposure

Use a water resistant sunscreen if swimming or sweating

Reapply at least every 2 hours
Children under 6 months of age: Ask a doctor

Inactive ingredients:

Coconut Oil, Sunflower Oil, Shea Butter, Ozokerite Wax, Beeswax, Flavor, Cornmint Oil, Stevia, Tocopherol, Soybean Oil.

DOSAGE AND ADMINISTRATION

Applly liberally 15 minutes before sun exposure

INDICATIONS AND USAGE

Helps prevent sunburn